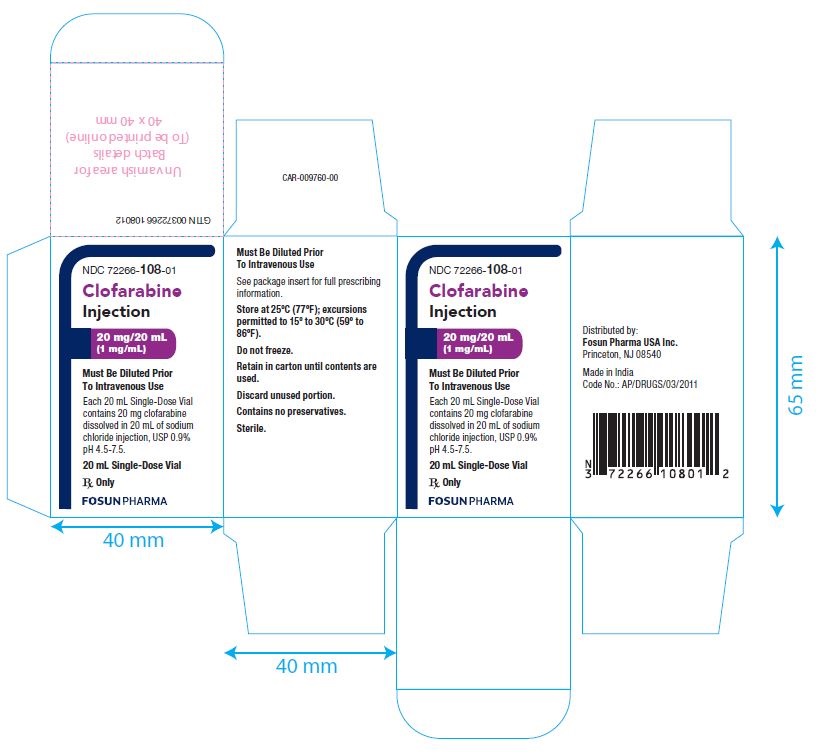 DRUG LABEL: CLOFARABINE
NDC: 72266-108 | Form: INJECTION
Manufacturer: Fosun Pharma USA Inc.
Category: prescription | Type: HUMAN PRESCRIPTION DRUG LABEL
Date: 20230215

ACTIVE INGREDIENTS: CLOFARABINE 1 mg/1 mL
INACTIVE INGREDIENTS: SODIUM CHLORIDE 9 mg/1 mL; WATER

HIGHLIGHTS OF PRESCRIBING INFORMATION

These highlights do not include all the information needed to use CLOFARABINE INJECTION safely and effectively. See full prescribing information for CLOFARABINE INJECTION.
CLOFARABINE injection, for intravenous use.
Initial U.S. Approval: 2004

RECENT MAJOR CHANGES

Indications and Usage (1) 7/2022

1 INDICATIONS AND USAGE

Clofarabine Injection is a nucleoside metabolic inhibitor indicated for the treatment of pediatric patients 1 to 21 years old with relapsed or refractory acute lymphoblastic leukemia after at least two prior regimens. (1)

2 DOSAGE AND ADMINISTRATION

- Administer the recommended pediatric dose of 52 mg/m2 as an intravenous infusion over 2 hours daily for 5 consecutive days of a 28-day cycle. Repeat cycles every 2-6 weeks. (2.1)
- Provide supportive care, such as intravenous infusion fluids,antihyperuricemic treatment, and alkalinization of urine throughout the 5 days of Clofarabine Injection administration to reduce the risk of tumor lysis and other adverse events. (2.1)
- Discontinue Clofarabine Injection if hypotension develops during the 5 days of administration. (2.1)
- Reduce the dose in patients with renal impairment. (2.1)
- Use dose modification for toxicity. (2.3)

3 DOSAGE FORMS AND STRENGTHS

20 mg/20 mL single-dose vial. (3)

4 CONTRAINDICATIONS

None. (4)

5 WARNINGS AND PRECAUTIONS

- Myelosuppression: May be severe and prolonged. Monitor complete blood counts and platelet counts during Clofarabine Injection therapy. (5.1)
- Hemorrhage: Serious and fatal cerebral, gastrointestinal and pulmonary hemorrhage. Monitor platelets and coagulation parameters and treat accordingly. (5.2)
- Infections: Severe and fatal sepsis as a result of bone marrow suppression. Monitor for signs and symptoms of infection; discontinue Clofarabine Injection and treat promptly. (5.3)
- Tumor Lysis syndrome: Anticipate, monitor for signs and symptoms and treat promptly. (5.4)
- Systemic Inflammatory Response Syndrome (SIRS) or Capillary Leak Syndrome: Monitor for and discontinue Clofarabine Injection immediately if
- suspected. (5.5)
- Venous Occlusive Disease of the Liver: Monitor for and discontinue Clofarabine Injection if suspected. (5.6)
- Hepatotoxicity: Severe and fatal hepatotoxicity. Monitor liver function, for signs and symptoms of hepatitis and hepatic failure. Discontinue Clofarabine Injection immediately for Grade 3 or greater liver enzyme and/or bilirubin elevations. (5.7)
- Renal Toxicity: Increased creatinine and acute renal failure; monitor renal function and interrupt or discontinue Clofarabine Injection. (5.8)
- Enterocolitis: Serious and fatal enterocolitis, occurring more frequently within 30 days of treatment and with combination chemotherapy. Monitor patients for signs and symptoms of enterocolitis and treat promptly. (5.9)
- Skin Reactions: Stevens-Johnson syndrome (SJS) and toxic epidermal necrolysis (TEN), including fatal cases. Discontinue for exfoliative or bullous rash, or if SJS or TEN is suspected. (5.10)

6 ADVERSE REACTIONS

Most common adverse reactions (≥25%): vomiting, nausea, diarrhea, febrile neutropenia, pruritus, headache, bacteremia, pyrexia, rash, tachycardia, abdominal pain, chills, fatigue, anorexia, pain in extremity, hypotension, epistaxis, and petechiae. (6)

To report SUSPECTED ADVERSE REACTIONS, contact Fosun Pharma USA Inc. at 1-866-611-3762 or FDA at 1-800-FDA-1088 or www.fda.gov/medwatch.

8 USE IN SPECIFIC POPULATIONS

- Embryo-fetal Toxicity: fetal harm can occur when administered to a pregnant woman. Women should be advised to avoid becoming pregnant when receiving Clofarabine Injection. (5.11, 8.1)

See 17 for PATIENT COUNSELING INFORMATION

FULL PRESCRIBING INFORMATION

1 INDICATIONS AND USAGE

Clofarabine Injection is indicated for the treatment of pediatric patients 1 to 21 years old with relapsed or refractory acute lymphoblastic leukemia after at least two prior regimens.

2 DOSAGE AND ADMINISTRATION

2.1 Recommended Dosage

Administer the recommended pediatric dose of 52 mg/m2 as an intravenous infusion over 2 hours daily for 5 consecutive days.

- Treatment cycles are repeated following recovery or return to baseline organ function, approximately every 2 to 6 weeks. The dosage is based on the patient’s body surface area (BSA), calculated using the actual height and weight before the start of each cycle. To prevent drug incompatibilities, no other medications should be administered through the same intravenous line.
- Provide supportive care, such as intravenous fluids, antihyperuricemic treatment, and alkalinize urine throughout the 5 days of Clofarabine Injection administration to reduce the effects of tumor lysis and other adverse events.
- Discontinue Clofarabine Injection if hypotension develops during the 5 days of administration.
- Monitor renal and hepatic function during the 5 days of Clofarabine Injection administration [see Warnings and Precautions (5.7, 5.8)].
- Monitor patients taking medications known to affect blood pressure. Monitor cardiac function during administration of Clofarabine Injection.
- Reduce the dose by 50% in patients with creatinine clearance (CrCL) between 30 and 60 mL/min. There is insufficient information to make a dosage recommendation in patients with CrCL less than 30 mL/min [see Use in Specific Populations (8.7)].

2.2 Supportive Medications and Medications to Avoid

- Consider prophylactic anti-emetic medications as Clofarabine Injection is moderately emetogenic.
- Consider the use of prophylactic steroids to mitigate Systemic Inflammatory Response Syndrome (SIRS) or capillary leak syndrome (e.g., hypotension, tachycardia, tachypnea, and pulmonary edema).
- Minimize exposure to drugs with known renal toxicity during the 5 days of Clofarabine Injection administration since the risk of renal toxicity may be increased.
- Consider avoiding concomitant use of medications known to induce hepatic toxicity.

2.3 Dose Modifications and Reinitiation of Therapy

Hematologic Toxicity

- Administer subsequent cycles no sooner than 14 days from the starting day of the previous cycle and provided the patient’s ANC is ≥0.75 × 10^9/L.
- If a patient experiences a Grade 4 neutropenia (ANC <0.5 × 10^9/L) lasting ≥4 weeks, reduce dose by 25% for the next cycle.

Non-hematologic Toxicity

- Withhold Clofarabine Injection if a patient develops a clinically significant infection, until the infection is controlled, then restart at the full dose.
- Withhold Clofarabine Injection for a Grade 3 non-infectious non-hematologic toxicity (excluding transient elevations in serum transaminases and/or serum bilirubin and/or nausea/vomiting controlled by antiemetic therapy). Re-institute Clofarabine Injection administration at a 25% dose reduction when resolution or return to baseline.

2.4 Reconstitution/Preparation

Clofarabine Injection should be filtered through a sterile 0.2 micron syringe filter and then diluted with 5% Dextrose Injection, USP, or 0.9% Sodium Chloride Injection, USP, prior to intravenous (IV) infusion to a final concentration between 0.15 mg/mL and 0.4 mg/mL. Use within 24 hours of preparation. Store diluted Clofarabine Injection at room temperature (15-30ºC).

2.5 Incompatibility

Do not administer any other medications through the same intravenous line.

3 DOSAGE FORMS AND STRENGTHS

20 mg/20 mL (1 mg/mL) single-dose vial

4 CONTRAINDICATIONS

None

5 WARNINGS AND PRECAUTIONS

5.1 Myelosuppression

Clofarabine Injection causes myelosuppression which may be severe and prolonged. Febrile neutropenia occurred in 55% and non-febrile neutropenia in an additional 10% of pediatric patients in clinical trials. At initiation of treatment, most patients in the clinical studies had hematological impairment as a manifestation of leukemia. Myelosuppression is usually reversible with interruption of Clofarabine Injection treatment and appears to be dose-dependent. Monitor complete blood counts [see Dosage and Administration (2.3)].

5.2 Hemorrhage

Serious and fatal hemorrhage, including cerebral, gastrointestinal and pulmonary hemorrhage, has occurred. The majority of the cases were associated with thrombocytopenia. Monitor platelets and coagulation parameters and treat accordingly [see Adverse Reactions (6.2)].

5.3 Infections

Clofarabine Injection increases the risk of infection, including severe and fatal sepsis, and opportunistic infections. At baseline, 48% of the pediatric patients had one or more concurrent infections. A total of 83% of patients experienced at least one infection after Clofarabine Injection treatment, including fungal, viral and bacterial infections. Monitor patients for signs and symptoms of infection, discontinue Clofarabine Injection, and treat promptly.

5.4 Hyperuricemia (Tumor Lysis)

Administration of Clofarabine Injection may result in tumor lysis syndrome associated with the break-down metabolic products from peripheral leukemia cell death. Monitor patients undergoing treatment for signs and symptoms of tumor lysis syndrome and initiate preventive measures including adequate intravenous fluids and measures to control uric acid.

5.5 Systemic Inflammatory Response Syndrome (SIRS) and Capillary Leak Syndrome

Clofarabine Injection may cause a cytokine release syndrome (e.g., tachypnea, tachycardia, hypotension, pulmonary edema) that may progress to the systemic inflammatory response syndrome (SIRS) with capillary leak syndrome and organ impairment which may be fatal. Monitor patients frequently for these conditions. In clinical trials, SIRS was reported in two patients (2%); capillary leak syndrome was reported in four patients (4%). Symptoms included rapid onset of respiratory distress, hypotension, pleural and pericardial effusion, and multi-organ failure. Close monitoring for this syndrome and early intervention may reduce the risk. Immediately discontinue Clofarabine Injection and provide appropriate supportive measures. The use of prophylactic steroids (e.g., 100 mg/m2 hydrocortisone on Days 1 through 3) may be of benefit in preventing signs or symptoms of SIRS or capillary leak. Consider use of diuretics and/or albumin. After the patient is stabilized and organ function has returned to baseline, re-treatment with Clofarabine Injection can be considered with a 25% dose reduction.

5.6 Venous Occlusive Disease of the Liver

Patients who have previously received a hematopoietic stem cell transplant (HSCT) are at higher risk for veno-occlusive disease (VOD) of the liver following treatment with clofarabine (40 mg/m2) when used in combination with etoposide (100 mg/m2) and cyclophosphamide (440 mg/m2). Severe hepatotoxic events have been reported in a combination study of clofarabine in pediatric patients with relapsed or refractory acute leukemia. Two cases (2%) of VOD in the mono-therapy studies were considered related to study drug. Monitor for and discontinue Clofarabine Injection if VOD is suspected.

5.7 Hepatotoxicity

Severe and fatal hepatotoxicity, including hepatitis and hepatic failure, has occurred with the use of Clofarabine Injection [see Adverse Reactions (6.2)]. In clinical studies, Grade 3-4 liver enzyme elevations were observed in pediatric patients during treatment with Clofarabine Injection at the following rates: elevated aspartate aminotransferase (AST) occurred in 36% of patients; elevated alanine aminotransferase (ALT) occurred
in 44% of patients. AST and ALT elevations typically occurred within 10 days of Clofarabine Injection administration and returned to Grade 2 or less within 15 days. Grade 3 or 4 elevated bilirubin occurred in 13% of patients, with 2 events reported as Grade 4 hyperbilirubinemia (2%), one of which resulted in treatment discontinuation and one patient had multi-organ failure and died. Eight patients (7%) had Grade 3 or 4 elevations in serum bilirubin at the last time point measured; these patients died due to sepsis and/or multi-organ failure. Monitor hepatic function and for signs and symptoms of hepatitis and hepatic failure. Discontinue Clofarabine Injection immediately for Grade 3 or greater liver enzyme and/or bilirubin elevations [see Adverse Reactions (6.1)].

5.8 Renal Toxicity

Clofarabine Injection may cause acute renal failure. In Clofarabine Injection treated patients in clinical studies, Grade 3 or 4 elevated creatinine occurred in 8% of patients and acute renal failure was reported as Grade 3 in three patients (3%) and Grade 4 in two patients (2%). Patients with infection, sepsis, or tumor lysis syndrome may be at increased risk of renal toxicity when treated with Clofarabine Injection. Hematuria
occurred in 13% of Clofarabine Injection treated patients overall. Monitor patients for renal toxicity and interrupt or discontinue Clofarabine Injection as necessary [see Adverse Reactions (6.1)].

5.9 Enterocolitis

Fatal and serious cases of enterocolitis, including neutropenic colitis, cecitis, and C. difficile colitis, have occurred during treatment with clofarabine. This has occurred more frequently within 30 days of treatment, and in the setting of combination chemotherapy. Enterocolitis may lead to necrosis, perforation, hemorrhage or sepsis complications. Monitor patients for signs and symptoms of enterocolitis and treat promptly [see Adverse Reactions (6.2)].

5.10 Skin Reactions

Serious and fatal cases of Stevens-Johnson syndrome (SJS) and toxic epidermal necrolysis (TEN), have been reported. Discontinue Clofarabine for exfoliative or bullous rash, or if SJS or TEN is suspected [see Adverse Reactions (6.2)].

5.11 Embryo-fetal Toxicity

Clofarabine Injection can cause fetal harm when administered to a pregnant woman. Intravenous doses of clofarabine in rats and rabbits administered during organogenesis caused an increase in resorptions, malformations, and variations [see Use in Specific Populations (8.1)].

6 ADVERSE REACTIONS

The following adverse reactions are discussed in greater detail in other sections of the label:

- Myelosuppression [ see Warnings and Precautions (5.1)]
- Hemorrhage [ see Warnings and Precautions (5.2)]
- Serious Infections [ see Warnings and Precautions (5.3)]
- Hyperuricemia (Tumor Lysis) [ see Warnings and Precautions (5.4)]
- Systemic Inflammatory Response Syndrome (SIRS) and Capillary Leak Syndrome [ see Warnings and Precautions (5.5)]
- Venous Occlusive Disease of the Liver [ see Warnings and Precautions (5.6)]
- Hepatotoxicity [ see Warnings and Precautions (5.7)]
- Renal Toxicity [ see Warnings and Precautions (5.8)]
- Enterocolitis [ see Warnings and Precautions (5.9)]
- Skin Reactions [ see Warnings and Precautions (5.10)]

6.1 Clinical Trials Experience

Because clinical trials are conducted under widely varying conditions, adverse reaction rates observed in the clinical trials of a drug cannot be directly compared to rates in the clinical trials of another drug and may not reflect the rates observed in practice. The data described below reflect exposure to Clofarabine Injection in 115 pediatric patients with relapsed or refractory Acute Lymphoblastic Leukemia (ALL) (70 patients) or Acute Myelogenous Leukemia (AML) (45 patients).

In total, 115 pediatric patients treated in clinical trials received the recommended dose of Clofarabine Injection 52 mg/m2 daily × 5. The median number of cycles was 2. The median cumulative amount of Clofarabine Injection received by pediatric patients during all cycles was 540 mg.

Most common adverse reactions (≥25%): vomiting, nausea, diarrhea, febrile neutropenia, pruritus, headache, bacteremia, pyrexia, rash, tachycardia, abdominal pain, chills, fatigue, anorexia, pain in extremity, hypotension, epistaxis, and petechiae. Table 1 lists adverse reactions by System Organ Class, including severe or life-threatening (NCI CTC Grade 3 or Grade 4), reported in ≥5% of the 115 patients in the 52 mg/m2/day dose group (pooled analysis of pediatric patients with ALL and AML). More detailed information and follow-up of certain events is given below.

Table 1: Most Commonly Reported (≥5% Overall) Adverse Reactions by System Organ Class (N=115 pooled analysis)
System Organ Class¹ | Preferred Term¹ | ALL/AM (N=115) |  | Worst NCI Common Terminology Criteria Grade¹
System Organ Class¹ | Preferred Term¹ | ALL/AM (N=115) |  | 3 |  | 4 |  | 5
System Organ Class¹ | Preferred Term¹ | N | % | N | % | N | % | N | %
Blood and Lymphatic System Disorders | Febrile neutropenia | 63 | 55 | 59 | 51 | 3 | 3
Blood and Lymphatic System Disorders | Neutropenia | 11 | 10 | 3 | 3 | 8 | 7 | . | .
Cardiac Disorders | Pericardial effusion | 9 | 8 | . | . | 1 | 1 | . | .
Cardiac Disorders | Tachycardia | 40 | 35 | 6 | 5 | . | . | . | .
Gastrointestinal Disorders | Abdominal pain | 40 | 35 | 8 | 7 | . | . | . | .
Gastrointestinal Disorders | Abdominal pain upper | 9 | 8 | 1 | 1 | . | . | . | .
Gastrointestinal Disorders | Diarrhea | 64 | 56 | 14 | 12 | . | . | . | .
Gastrointestinal Disorders | Gingival or mouth bleeding | 20 | 17 | 8 | 7 | 1 | 1 | . | .
Gastrointestinal Disorders | Nausea | 84 | 73 | 16 | 14 | 1 | 1 | . | .
Gastrointestinal Disorders | Oral mucosal petechiae | 6 | 5 | 4 | 4 | . | . | . | .
Gastrointestinal Disorders | Proctalgia | 9 | 8 | 2 | 2 | . | . | . | .
Gastrointestinal Disorders | Stomatitis | 8 | 7 | 1 | 1 | . | . | . | .
Gastrointestinal Disorders | Vomiting | 90 | 78 | 9 | 8 | 1 | 1 | . | .
General Disorders and Administration Site Conditions | Asthenia | 12 | 10 | 1 | 1 | 1 | 1 | . | .
General Disorders and Administration Site Conditions | Chills | 39 | 34 | 3 | 3 | . | . | . | .
General Disorders and Administration Site Conditions | Fatigue | 39 | 34 | 3 | 3 | 2 | 2 | . | .
General Disorders and Administration Site Conditions | Irritability | 11 | 10 | 1 | 1 | . | . | . | .
General Disorders and Administration Site Conditions | Mucosal inflammation | 18 | 16 | 2 | 2 | . | . | . | .
General Disorders and Administration Site Conditions | Edema | 14 | 12 | 2 | 2 | . | . | . | .
General Disorders and Administration Site Conditions | Pain | 17 | 15 | 7 | 6 | 1 | 1 | . | .
General Disorders and Administration Site Conditions | Pyrexia | 45 | 39 | 16 | 14 | . | . | . | .
Hepatobiliary Disorder | Jaundice | 9 | 8 | 2 | 2 | . | . | . | .
Infections and Infestations | Bacteremia | 10 | 9 | 10 | 9 | . | . | . | .
Infections and Infestations | Candidiasis | 8 | 7 | 1 | 1 | . | . | . | .
Infections and Infestations | Catheter related infection | 14 | 12 | 13 | 11 | . | . | . | .
Infections and Infestations | Cellulitis | 9 | 8 | 7 | 6 | . | . | . | .
Infections and Infestations | Clostridium colitis | 8 | 7 | 6 | 5 | . | . | . | .
Infections and Infestations | Herpes simplex | 11 | 10 | 6 | 5 | . | . | . | .
Infections and Infestations | Herpes zoster | 8 | 7 | 6 | 5 | . | . | . | .
Infections and Infestations | Oral candidiasis | 13 | 11 | 2 | 2 | . | . | . | .
Infections and Infestations | Pneumonia | 11 | 10 | 6 | 5 | 1 | 1 | 1 | 1

¹ Patients with more than one preferred term within a SOC are counted only once in the SOC totals. Patients with more than one occurrence of the same preferred term are counted only once within that term and at the highest severity grade.

Table 1: Most Commonly Reported (≥5% Overall) Adverse Reactions by System Organ Class (N=115 pooled analysis) (Continued)
System Organ Class¹ | Preferred Term¹ | ALL/AML (N=115) |  | Worst NCI Common Terminology Criteria Grade¹
System Organ Class¹ | Preferred Term¹ | ALL/AML (N=115) |  | 3 |  | 4 |  | 5
System Organ Class¹ | Preferred Term¹ | N | % | N | % | N | % | N | %
Infections and Infestations (continued) | Sepsis, including septic shock | 19 | 17 | 6 | 5 | 4 | 4 | 9 | 8
Infections and Infestations (continued) | Staphylococcal bacteremia | 7 | 6 | 5 | 4 | 1 | 1 | . | .
Infections and Infestations (continued) | Staphylococcal sepsis | 6 | 5 | 5 | 4 | 1 | 1 | . | .
Infections and Infestations (continued) | Upper respiratory tract infection | 6 | 5 | 1 | 1 | . | . | . | .
Metabolism and Nutrition Disorders | Anorexia | 34 | 30 | 6 | 5 | 8 | 7 | . | .
Musculoskeletal and Connective Tissue Disorders | Arthralgia | 10 | 9 | 3 | 3 | . | . | . | .
Musculoskeletal and Connective Tissue Disorders | Back pain | 12 | 10 | 3 | 3 | . | . | . | .
Musculoskeletal and Connective Tissue Disorders | Bone pain | 11 | 10 | 3 | 3 | . | . | . | .
Musculoskeletal and Connective Tissue Disorders | Myalgia | 16 | 14 | . | . | . | . | . | .
Musculoskeletal and Connective Tissue Disorders | Pain in extremity | 34 | 30 | 6 | 5 | . | . | . | .
Neoplasms Benign, Malignant and Unspecified (incl. cysts and polyps) | Tumor lysis syndrome | 7 | 6 | 7 | 6 | . | . | . | .
Nervous System Disorders | Headache | 49 | 43 | 6 | 5 | . | . | . | .
Nervous System Disorders | Lethargy | 12 | 10 | 1 | 1 | . | . | . | .
Nervous System Disorders | Somnolence | 11 | 10 | 1 | 1 | . | . | . | .
Psychiatric Disorders | Agitation | 6 | 5 | 1 | 1 | . | . | . | .
Psychiatric Disorders | Anxiety | 24 | 21 | 2 | 2 | . | . | . | .
Renal and Urinary Disorders | Hematuria | 15 | 13 | 2 | 2 | . | . | . | .
Respiratory, Thoracic and Mediastinal Disorders | Dyspnea | 15 | 13 | 6 | 5 | 2 | 2 | . | .
Respiratory, Thoracic and Mediastinal Disorders | Epistaxis | 31 | 27 | 15 | 13 | . | . | . | .
Respiratory, Thoracic and Mediastinal Disorders | Pleural effusion | 14 | 12 | 4 | 4 | 2 | 2 | . | .
Respiratory, Thoracic and Mediastinal Disorders | Respiratory distress | 12 | 10 | 5 | 4 | 4 | 4 | 1 | 1
Respiratory, Thoracic and Mediastinal Disorders | Tachypnea | 10 | 9 | 4 | 4 | 1 | 1 | . | .
Skin and Subcutaneous Tissue Disorders | Erythema | 13 | 11 | . | . | . | . | . | .
Skin and Subcutaneous Tissue Disorders | Palmar-plantar erythrodysesthesia syndrome | 18 | 16 | 8 | 7 | . | . | . | .
Skin and Subcutaneous Tissue Disorders | Petechiae | 30 | 26 | 7 | 6 | . | . | . | .
Skin and Subcutaneous Tissue Disorders | Pruritus | 49 | 43 | 1 | 1 | . | . | . | .
Skin and Subcutaneous Tissue Disorders | Rash | 44 | 38 | 8 | 7 | . | . | . | .
Skin and Subcutaneous Tissue Disorders | Rash pruritic | 9 | 8 | . | . | . | . | . | .
Vascular Disorders | Flushing | 22 | 19 | . | . | . | . | . | .
Vascular Disorders | Hypertension | 15 | 13 | 6 | 5 | . | . | . | .
Vascular Disorders | Hypotension | 33 | 29 | 13 | 11 | 9 | 8 | . | .

¹ Patients with more than one preferred term within a SOC are counted only once in the SOC totals. Patients with more than one occurrence of the same preferred term are counted only once within that term and at the highest severity grade.

The following less common adverse reactions have been reported in 1-4% of the 115 pediatric patients with ALL or AML:

Gastrointestinal Disorders: cecitis, pancreatitis

Hepatobiliary Disorders: hyperbilirubinemia Immune System Disorders: hypersensitivity

Infections and Infestations: bacterial infection, Enterococcal bacteremia, Escherichia bacteremia, Escherichia sepsis, fungal infection, fungal sepsis, gastroenteritis adenovirus, infection, influenza, parainfluenza virus infection, pneumonia fungal, pneumonia primary atypical, Respiratory syncytial virus infection, sinusitis, staphylococcal infection

Investigations: blood creatinine increased

Psychiatric Disorders: mental status change

Respiratory, Thoracic and Mediastinal Disorder: pulmonary edema

Table 2 lists the incidence of treatment-emergent laboratory abnormalities after Clofarabine Injection administration at 52 mg/m2 among pediatric patients with ALL and AML (N=115).

Table 2: Incidence of Treatment-Emergent Laboratory Abnormalities after Clofarabine Injection Administration
Parameter | Any Grade | Grade 3 or higher
Anemia (N=114) | 83% | 75%
Leukopenia (N=114) | 88% | 88%
Lymphopenia (N=113) | 82% | 82%
Neutropenia (N=113) | 64% | 64%
Thrombocytopenia (N=114) | 81% | 80%
Elevated Creatinine (N=115) | 50% | 8%
Elevated SGOT (N=100) | 74% | 36%
Elevated SGPT (N=113) | 81% | 43%
Elevated Total Bilirubin (N=114) | 45% | 13%

6.2 Postmarketing Experience

The following adverse reactions have been identified during post-approval use of Clofarabine Injection. Because these reactions are reported voluntarily from a population of uncertain size, it is not always possible to reliably estimate their frequency or establish a causal relationship to drug exposure. Decisions to include these reactions in labeling are typically based on one or more of the following factors: (1) seriousness of the reaction, (2) reported frequency of the reaction, or (3) strength of causal connection to Clofarabine Injection.

- Gastrointestinal disorders: Gastrointestinal hemorrhage including fatalities.
- Metabolism and nutrition disorders: hyponatremia.
- Skin and subcutaneous tissue disorders: Stevens-Johnson Syndrome (SJS), toxic epidermal necrolysis (TEN) (including fatal cases).

8 USE IN SPECIFIC POPULATIONS

8.1 Pregnancy

Pregnancy Category D

Clofarabine Injection may cause fetal harm when administered to a pregnant woman. Clofarabine was teratogenic in rats and rabbits. Developmental toxicity (reduced fetal body weight and increased post-implantation loss) and increased incidences of malformations and variations (gross external, soft tissue, skeletal and retarded ossification) were observed in rats receiving 54 mg/m^2/day (approximately equivalent to the recommended clinical dose on a mg/m^2 basis), and in rabbits receiving 12 mg/m^2/day (approximately 23% of the recommended clinical dose on a mg/m^2 basis).

There are no adequate and well-controlled studies in pregnant women using clofarabine. If this drug is used during pregnancy, or if the patient becomes pregnant while taking this drug, the patient should be apprised of the potential hazard to the fetus.

Women of childbearing potential should be advised to avoid becoming pregnant while receiving treatment with clofarabine. All patients should be advised to use effective contraceptive measures to prevent pregnancy.

8.3 Nursing Mothers

It is not known whether clofarabine or its metabolites are excreted in human milk. Because of the potential for tumorigenicity shown for clofarabine in animal studies and the potential for serious adverse reactions, women treated with clofarabine should not nurse. Female patients should be advised to avoid breastfeeding during treatment with Clofarabine Injection.

8.4 Pediatric Use

Safety and effectiveness have been established in pediatric patients 1 to 21 years old with relapsed or refractory acute lymphoblastic leukemia.

8.5 Geriatric Use

Safety and effectiveness of Clofarabine Injection has not been established in geriatric patients aged 65 and older.

8.6 Adults with Hematologic Malignancies

Safety and effectiveness have not been established in adults.

8.7 Renal Impairment

Reduce the Clofarabine Injection starting dose by 50% in patients with CrCL of 30 to 60 mL/min. There is insufficient information to make a dosage recommendation in patients with CrCL less than 30 mL/min or in patients on dialysis.

The pharmacokinetics of clofarabine in patients with renal impairment and normal renal function were obtained from a population pharmacokinetic analysis of three pediatric and two adult studies. In patients with CrCL 60 to less than 90 mL/min (N=47) and CrCL 30 to less than 60 mL/min (N=30), the average AUC of clofarabine increased by 60% and 140%, respectively, compared to patients with normal (N=66) renal function (CrCL greater than 90 mL/min).

10 OVERDOSAGE

There were no known overdoses of Clofarabine Injection. The highest daily dose administered to a human to date (on a mg/m^2
basis) has been 70 mg/m^2/day × 5 days (2 pediatric ALL patients). The toxicities included in these 2 patients included Grade 4 hyperbilirubinemia, Grade 2 and 3 vomiting, and Grade 3 maculopapular rash.
In a Phase 1 study of adults with refractory and/or relapsed hematologic malignancies, the recommended pediatric dose of 52 mg/m^2/day was not tolerated.

11 DESCRIPTION

Clofarabine Injection contains clofarabine, a purine nucleoside metabolic inhibitor. Clofarabine Injection (1 mg/mL) is supplied in a 20 mL, single-dose vial. The 20 mL vial contains 20 mg clofarabine formulated in 20 mL unbuffered normal saline (comprised of Water for Injection, USP, and Sodium Chloride, USP). The pH range of the solution is 4.5 to 7.5. The solution is sterile, clear and practically colorless, and is preservative-free.

12 CLINICAL PHARMACOLOGY

12.1 Mechanism of Action

Clofarabine is sequentially metabolized intracellularly to the 5’-monophosphate metabolite by deoxycytidine kinase and mono- and di-phospho-kinases to the active 5’-triphosphate metabolite. Clofarabine has affinity for the activating phosphorylating enzyme, deoxycytidine kinase, equal to or greater than that of the natural substrate, deoxycytidine. Clofarabine inhibits DNA synthesis by decreasing cellular deoxynucleotide triphosphate pools through an inhibitory action on ribonucleotide reductase, and by terminating DNA chain elongation and inhibiting repair through incorporation into the DNA chain by competitive inhibition of DNA polymerases. The affinity of clofarabine triphosphate for these enzymes is similar to or greater than that of deoxyadenosine triphosphate. In preclinical models, clofarabine has demonstrated the ability to inhibit DNA repair by incorporation into the DNA chain during the repair process. Clofarabine 5’- triphosphate also disrupts the integrity of mitochondrial membrane, leading to the release of the pro-apoptotic mitochondrial proteins, cytochrome C and apoptosis-inducing factor, leading to programmed cell death.

Clofarabine is cytotoxic to rapidly proliferating and quiescent cancer cell types in vitro.

12.3 Pharmacokinetics

The population pharmacokinetics of Clofarabine Injection were studied in 40 pediatric patients aged 2 to 19 years (21 males/19 females) with relapsed or refractory acute lymphoblastic leukemia (ALL) or acute myelogenous leukemia (AML). At the given 52 mg/m^2 dose, similar concentrations were obtained over a wide range of body surface areas (BSAs). Clofarabine was 47% bound to plasma proteins, predominantly
to albumin. Based on non-compartmental analysis, systemic clearance and volume of distribution at steady-state were 28.8 L/h/m^2 and 172 L/m^2, respectively. The terminal half-life was 5.2 hours. No apparent difference in pharmacokinetics was observed between patients with ALL and AML or between males and females.

No relationship between clofarabine or clofarabine triphosphate exposure and toxicity or response was found in this population.

Based on 24-hour urine collections in the pediatric studies, 49-60% of the dose is excreted in the urine unchanged. In vitro studies using isolated human hepatocytes indicate very limited metabolism (0.2%). The pathways of non-hepatic elimination remain unknown.

Clofarabine has not been studied in patients with hepatic impairment.

Drug-Drug Interactions

In vitro studies suggested that clofarabine undergoes limited metabolism and does not inhibit or induce major CYP enzymes. CYP inhibitors and inducers are unlikely to affect the metabolism of clofarabine. Clofarabine is unlikely to affect the metabolism of CYP substrates. However, no in vivo drug interaction studies have been conducted. An in vitro transporter study suggested that clofarabine is a substrate of human transporters OAT1, OAT3, and OCT1. A preclinical study using perfused rat kidney demonstrated that the renal excretion of clofarabine was decreased by cimetidine, an inhibitor of the hOCT2. Although the clinical implications of this finding have not been determined, signs of Clofarabine Injection toxicity should be monitored when administered with other hOAT1, hOAT3, hOCT1 and hOCT2 substrates or inhibitors.

13 NONCLINICAL TOXICOLOGY

13.1 Carcinogenesis, Mutagenesis, Impairment of Fertility

Clofarabine has not been tested for carcinogenic potential.

Clofarabine showed clastogenic activity in the in vitro mammalian cell chromosome aberration assay (CHO cells) and in the in vivo rat micronucleus assay. It did not show evidence of mutagenic activity in the bacterial mutation assay (Ames test).

Studies in mice, rats, and dogs have demonstrated dose-related adverse effects on male reproductive organs. Seminiferous tubule and testicular degeneration and atrophy were reported in male mice receiving intraperitoneal (IP) doses of 3 mg/kg/day (9 mg/m^2/day, approximately 17% of clinical recommended dose on a mg/m^2 basis). The testes of rats receiving 25 mg/kg/day (150 mg/m^2/day, approximately 3 times the recommended clinical dose on a mg/m^2 basis) in a 6-month IV study had bilateral degeneration of the seminiferous epithelium with retained spermatids and atrophy of interstitial cells. In a 6-month IV dog study, cell degeneration of the epididymis and degeneration of the seminiferous epithelium in the testes were observed in dogs receiving 0.375 mg/kg/day (7.5 mg/m^2/day, approximately 14% of the clinical recommended dose on a mg/m^2 basis). Ovarian atrophy or degeneration and uterine mucosal apoptosis were observed in female mice at 75 mg/kg/day (225 mg/m^2/day, approximately 4-fold of recommended human dose on a mg/m^2 basis), the only dose administered to female mice. The effect on human fertility is unknown.

14 CLINICAL STUDIES

Seventy-eight (78) pediatric patients with ALL were exposed to Clofarabine Injection. Seventy (70) of the patients received the recommended pediatric dose of Clofarabine Injection 52 mg/m^2 daily for 5 days as an intravenous (IV) infusion.

Dose Escalation Study in Pediatric Patients with Hematologic Malignancies

The safety and efficacy of Clofarabine Injection were evaluated in pediatric patients with refractory or relapsed hematologic malignancies in an open-label, dose-escalation, noncomparative study. The starting dose of Clofarabine Injection was 11.25 mg/m^2/day IV infusion daily × 5 and escalated to 70 mg/m^2/day IV infusion daily × 5. This dosing schedule was repeated every 2 to 6 weeks depending on toxicity and response. Nine of 17 ALL patients were treated with Clofarabine Injection 52 mg/m^2 daily for 5 days. In the 17 ALL patients there were 2 complete remissions (12%) and 2 partial remissions (12%) at varying doses. Dose-limiting toxicities (DLTs) in this study were reversible hyperbilirubinemia and elevated transaminase levels and skin rash, experienced at 70 mg/m^2. As a result of this study, the recommended dose for subsequent study in pediatric patients was determined to be 52 mg/m^2/day for 5 days.

Single-Arm Study in Pediatric ALL

Clofarabine Injection was evaluated in an open-label, single-arm study of 61 pediatric patients with relapsed/refractory ALL. Patients received a dose of 52 mg/m^2 over 2 hours for 5 consecutive days repeated every 2 to 6 weeks for up to 12 cycles. There was no dose escalation in this study.

All patients had disease that had relapsed after and/or was refractory to two or more prior therapies. Most patients, 38/61 (62%), had received >2 prior regimens and 18/61 (30%) of the patients had undergone at least 1 prior transplant. The median age of the treated patients was 12 years, 61% were male, 39% were female, 44% were Caucasian, 38% were Hispanic, 12% were African-American, 2% were Asian and 5% were Other race.

The overall remission (OR) rate (Complete Remission [CR] + CR in the absence of total platelet recovery [CRp]) was evaluated. CR was defined as no evidence of circulating blasts or extramedullary disease, an M1 bone marrow (≤5% blasts), and recovery of peripheral counts [platelets ≥100 × 10^9/L and absolute neutrophil count (ANC) ≥1.0 × 10^9/L]. CRp was defined as meeting all criteria for CR except for recovery of platelet counts to ≥100 × 10^9/L. Partial Response (PR) was also determined, defined as complete disappearance of circulating blasts, an M2 bone marrow (≥5% and ≤25% blasts), and appearance of normal progenitor cells or an M1 marrow that did not qualify for CR or CRp. Duration of remission was also evaluated.

Transplantation rate was not a study endpoint.

Response rates for these studies were determined by an unblinded Independent Response Review Panel (IRRP).

Table 3 summarizes results for the pediatric ALL study. Responses were seen in both pre-B and T-cell immunophenotypes of ALL. The median cumulative dose was 530 mg (range 29-2815 mg) in 1 (41%), 2 (44%) or 3 or more (15%) cycles. The median number of cycles was 2 (range 1-12). The median time between cycles was 28 days with a range of 12 to 55 days.

Table 3: Results in Single-Arm Pediatric ALL
 | N=61
CR % [95% CI] | 11.5 (4.7, 22.2)
CRp % [95% CI] | 8.2 (2.7, 18.1)
Median Duration of CR plus CRp (range in weeks)1 | 10.7 (4.3 to 58.6)

CR = Complete response

CRp = Complete response without platelet recovery

^1 Does not include 4 patients who were transplanted (duration of response, including response after transplant, in these 4 patients was 28.6 to 107.7 weeks).

Six (9.8%) patients achieved a PR; the clinical relevance of a PR in this setting is unknown.

Of 35 patients who were refractory to their immediately preceding induction regimen, 6 (17%) achieved a CR or CRp. Of 18 patients who had at least 1 prior hematopoietic stem cell transplant (HSCT), 5 (28%) achieved a CR or CRp.

Among the 12 patients who achieved at least a CRp, 6 patients achieved the best response after 1 cycle of clofarabine, 5 patients required 2 courses and 1 patient achieved a CR after 3 cycles of therapy.

15 REFERENCES

1. OSHA Hazardous Drugs. OSHA. http://www.osha.gov/SLTC/hazardousdrugs/index.html.

16 HOW SUPPLIED/STORAGE AND HANDLING

Clofarabine Injection is supplied in single-dose flint vials containing 20 mg of clofarabine in 20 mL of solution. Each box contains one Clofarabine Injection vial (NDC 72266-108-01). The 20 mL flint vials contain 20 mL (20 mg) of solution. The pH range of the solution is 4.5 to 7.5.

Vials containing undiluted Clofarabine Injection should be stored at 25°C (77°F); excursions permitted to 15 - 30°C (59 - 86°F).

Diluted admixtures may be stored at room temperature, but must be used within 24 hours of preparation.

Procedures for proper handling and disposal should be utilized. Handling and disposal of Clofarabine Injection should conform to guidelines issued for cytotoxic drugs. Several guidelines on this subject have been published.^1

17 PATIENT COUNSELING INFORMATION

Hematologic Toxicity: Advise patients to return for regular blood counts and to report any symptoms associated with hematologic toxicity (such as weakness, fatigue, pallor, shortness of breath, easy bruising, petechiae, purpura, fever) to their physician [ see Warnings and Precautions (5.1), Adverse Reactions (6.1)].

Infection: Advise patients of the signs or symptoms of infection (e.g., fever) and report to the physician immediately if any occur [ see Warnings and Precautions (5.3), Adverse Reactions (6.1)].

Hepatic and Renal Toxicity: Advise patients to avoid medications including over the counter and herbal medications, which may be hepatotoxic or nephrotoxic, during the 5 days of Clofarabine Injection administration. Also, advise patients of the possibility of developing liver function abnormalities and to immediately report signs or symptoms of jaundice. Advise patients of the signs or symptoms of renal failure/ acute renal failure [ see Warnings and Precautions (5.7, 5.8)].

Systemic Inflammatory Response Syndrome (SIRS)/Capillary Leak Syndrome: Advise patients of the signs or symptoms of SIRS, such as fever, tachycardia, tachypnea, dyspnea and symptoms suggestive of hypotension [ see Warnings and Precautions (5.5), Adverse Reactions (6.1)].

Pregnancy and Breastfeeding: Advise male and female patients with reproductive potential to use effective contraceptive measures to prevent pregnancy [ see Warnings and Precautions(5.11), Use in Specific Populations (8.1)]. Advise female patients to avoid breastfeeding during Clofarabine Injection treatment [ see Use in Specific Populations (8.3)].

Gastrointestinal Disorders: Advise patients that they may experience nausea, vomiting, and/or diarrhea with Clofarabine Injection. If these symptoms are significant, they should seek medical attention [ see Warnings and Precautions (5.9)].

Rash: Advise patients that they may experience skin rash with Clofarabine Injection. If this symptom is significant, they should seek medical attention.

Distributed by:
Fosun Pharma USA Inc.
Princeton, NJ 08540

Made in India

Revised: February 2023

1313000323-02

PACKAGE LABEL

NDC 72266-108-01

Clofarabine Injection

20 mg/20 mL

(1 mg/mL)

Must Be Diluted Prior To Intravenous Use

Each 20 mL Single-Dose Vial contains 20 mg clofarabine dissolved in 20 mL of sodium chloride injection, USP 0.9% pH 4.5-7.5.

Rx only

20 mL Single-Dose Vial

FOSUN PHARMA